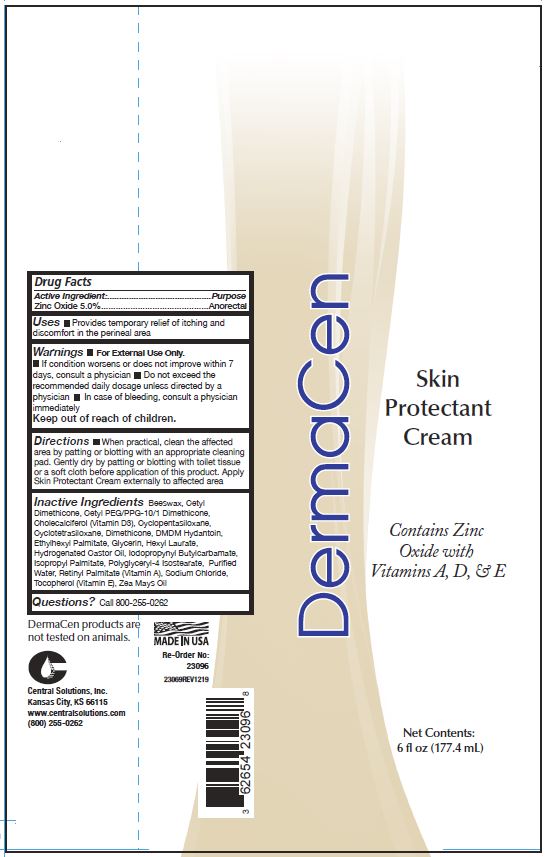 DRUG LABEL: DermaCen Skin Protectant
NDC: 62654-148 | Form: CREAM
Manufacturer: Central Solutions Inc
Category: otc | Type: HUMAN OTC DRUG LABEL
Date: 20241209

ACTIVE INGREDIENTS: ZINC OXIDE 50 mg/1 mL
INACTIVE INGREDIENTS: CETYL PEG/PPG-10/1 DIMETHICONE (HLB 2); CYCLOMETHICONE 5; CYCLOMETHICONE 4; DIMETHICONE; DMDM HYDANTOIN; ETHYLHEXYL PALMITATE; GLYCERIN; HEXYL LAURATE; POLYGLYCERYL-4 ISOSTEARATE; WATER; SODIUM CHLORIDE; TOCOPHEROL; CETYL DIMETHICONE 25; HYDROGENATED CASTOR OIL; VITAMIN A PALMITATE; CORN OIL; IODOPROPYNYL BUTYLCARBAMATE; ISOPROPYL PALMITATE; CHOLECALCIFEROL; YELLOW WAX

Drug Facts 62654-148

Active ingredient

Zinc Oxide 5.0%

Purpose

Anorectal

Uses

Provides temporary relief of itching and discomfort in the perineal area

Warnings

For External Use Only.

- If condition worsens or does not improve within 7 days, consult a physician
- Do not exceed the recommended daily dosage unless directed by a physician
- In case of bleeding, consult a physician immediately

Directions

When practical, clean the affected area by patting or blotting with an appropriate cleaning pad.

Gently dry by patting or blotting with toilet tissue or a soft cloth before application of this product.

Apply Skin Protectant Cream externally to affected area

Inactive ingredients

Beeswax, Cetyl Dimethicone, Cetyl PEG/PPG-10/1 Dimethicone, Cholecalciferol (Vitamin D3), Cyclopentasiloxane, Cyclotetrasiloxane, Dimethicone, DMDM Hydantoin, Ethylhexyl Palmitate, Glycerin, Hexyl Laurate, Hydrogenated Castor Oil, Iodopropynyl Butylcarbamate, Isopropyl palmitate, Polyglyceryl-4 Isostearate, Putified Water, Retinyl Palmitate (Vitamin A), Sodium Chloride, Tocopherol (Vitamin E), Zea Mays Oil

Questions?

Call 800-255-0262

Keep out of reach of children.

PACKAGE LABEL

DermaCen

Skin

Protectant

Cream

Conains Zinc

Oxide with

Vitamins A,D, and E

Net Contents:

6 fl oz (177.4 mL)

DCSPC label